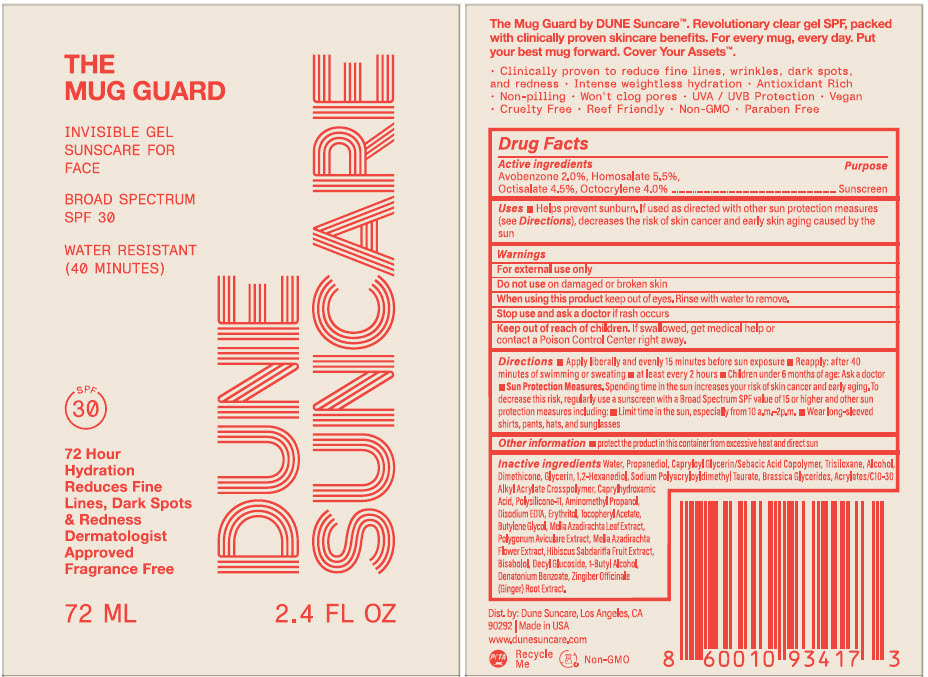 DRUG LABEL: The Mug Guard 
NDC: 82757-100 | Form: GEL
Manufacturer: Dune Suncare, Inc.
Category: otc | Type: HUMAN OTC DRUG LABEL
Date: 20240404

ACTIVE INGREDIENTS: Avobenzone 20 mg/1 mL; Homosalate 55 mg/1 mL; Octisalate 45 mg/1 mL; Octocrylene 40 mg/1 mL
INACTIVE INGREDIENTS: Water; Dimethicone; Propanediol; Alcohol; CAPRYLOYL GLYCERIN/SEBACIC ACID COPOLYMER (2000 MPA.S); 1,2-Hexanediol; Glycerin; TRISILOXANE; CARBOMER COPOLYMER TYPE A (ALLYL PENTAERYTHRITOL CROSSLINKED); Caprylhydroxamic Acid; Dimethicone/Vinyl Dimethicone Crosspolymer (Soft Particle); Aminomethylpropanol; Edetate Disodium Anhydrous; Erythritol; .Alpha.-Tocopherol Acetate; Butylene Glycol; AZADIRACHTA INDICA LEAF; Polygonum Aviculare Top; AZADIRACHTA INDICA FLOWER; TERT-BUTYL ALCOHOL; Levomenol; DENATONIUM BENZOATE; Decyl Glucoside; Ginger

The Mug Guard
Invisible Sunscreen for Face

DRUG FACTS

Active ingredients

Avobenzone 2.0%
Homosalate 5.5%
Octisalate 4.5%
Octocrylene 4.0%

Purpose

Sunscreen

Uses

- helps prevent sunburn
- if used as directed with other sun protection measures (see Directions), decrease the risk of skin cancer and early skin aging caused by the sun.

Warnings

For external use only

Do not use on damaged or broken skin

When using this product keep out of eyes. Rinse water to remove

Stop use and ask a doctor if rash occurs

Keep out of reach of children. If swallowed, get medical help or contact Poison Control Center right away.

Directions

- apply liberally and evenly 15 minutes before sun exposure
- reapply:
  - after 40 minutes of swimming or sweating.
  - at least every 2 hours
- children under 6 months of age: Ask a doctor
- Sun Protection Measures. Spending time in the sun increases your risk of skin cancer and early aging. To decrease this risk, regularly use a sunscreen with a Broad Spectrum SPF value of 15 or higher and other sun protection measures including:
  - limit time in the sun, especially from 10a.m.-2p.m.
  - wear long-sleeved shirts, pants, hats, and sunglasses

Other Information

- protect the product in this container from excessive heat and direct sun

Inactive ingredients

Water, Propanediol, Capryloyl Glycerin/Sebacic Acid Copolymer, Trisiloxane, Alcohol, Dimethicone, Glycerin, 1,2-Hexanediol, Sodium Polyacryloyldimethyl Taurate, Brassica Glycerides, Acrylates C10-30 Alkyl Acrylate Crosspolymer, Caprylhydroxamic Acid, Polysilicone-11, Aminomethyl Propanol, Disodium EDTA, Erythritol, Tocopheryl Acetate, Butylene Glycol, Melia Azadirachta Leaf Extract, Polygonum Aviculare Extract, Melia Azadirachta Flower Extract, Hibiscus Sabdariffa Fruit Extract, Bisabolol, Decyl Glucoside, t-Butyl Alcohol, Dentonium Benzoate, Zingiber Officinale (Ginger) Root Extract.

Dist. by: Dune Suncare, Los Angeles, CA 90292

PRINCIPAL DISPLAY PANEL - 72 ML Bottle Label

THE
MUG GUARD

INVISIBLE GEL
SUNSCARE FOR
FACE

BROAD SPECTRUM
SPF 30

WATER RESISTANT
(40 MINUTES)

SPF
30

72 Hour
Hydration
Reduces Fine
Lines, Dark Spots
& Redness
Dermatologist
Approved
Fragrance Free

72 ML
2.4 FL OZ

DUNE
SUNCARE